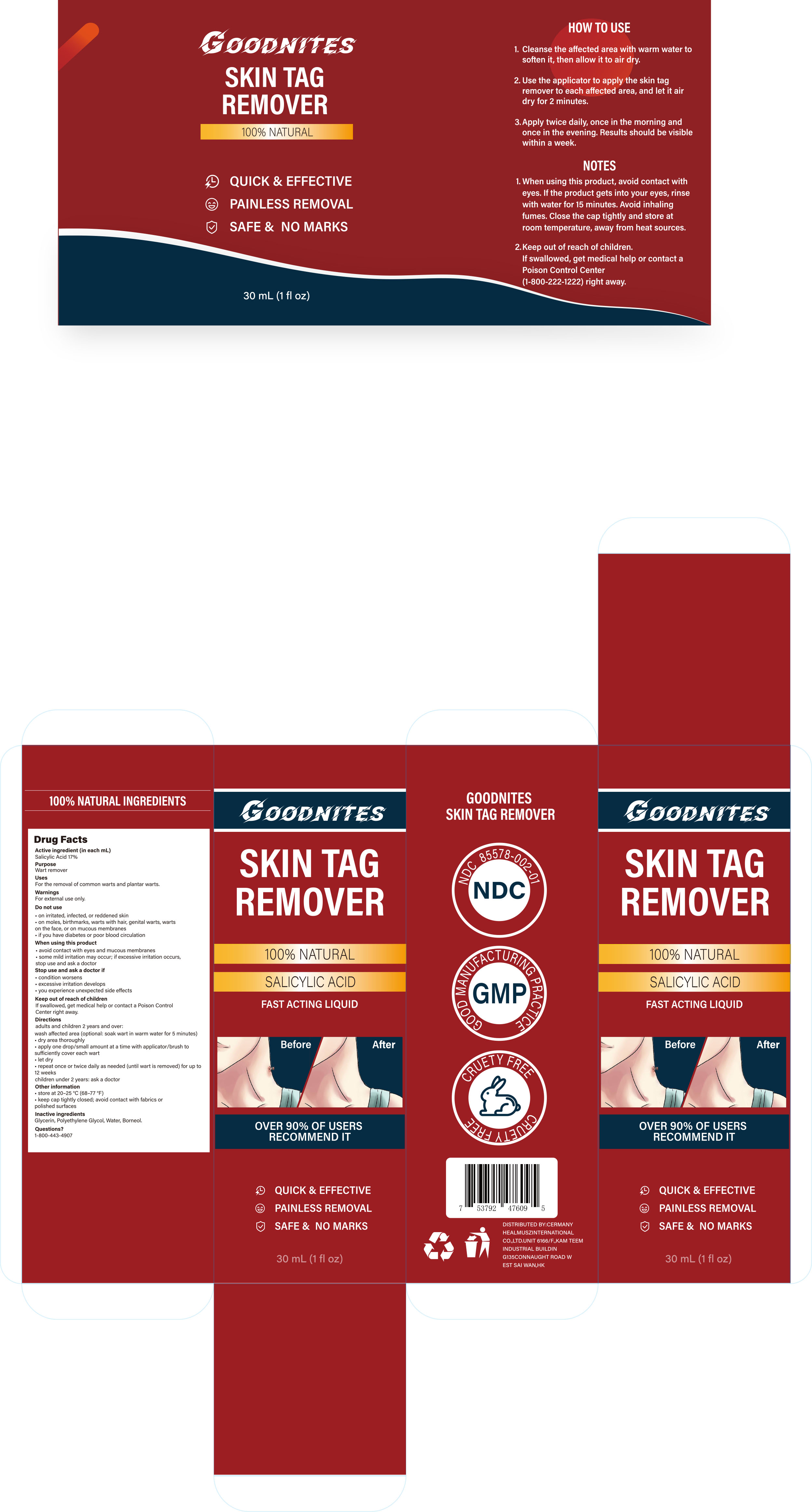 DRUG LABEL: Goodnites skin tag remover
NDC: 85578-002 | Form: LIQUID
Manufacturer: Zhengzhou Hangrui Network Technology Co., Ltd.
Category: otc | Type: HUMAN OTC DRUG LABEL
Date: 20250827

ACTIVE INGREDIENTS: SALICYLIC ACID 1.5 g/100 mL
INACTIVE INGREDIENTS: BORNEOL; WATER; GLYCERIN; POLYETHYLENE GLYCOL, UNSPECIFIED

85578-002 Goodnites skin tag remover

ACTIVE INGREDIENT

Salicylic Acid 17%

PURPOSE

Wart remover

KEEP OUT OF REACH OF CHILDREN

lf swallowed, get medical help or contact a Poison Control Center right away.

INDICATIONS AND USAGE

For the removal of common warts and plantar warts.

WARNINGS

For external use only.

WHEN USING

avoid contact with eyes and mucous membranes
some mild irritation may occur; if excessive irritation occurs stop use and ask a doctor

STOP USE

condition worsens
excessive irritation develops
you experience unexpected side effects

DO NOT USE

on irritated, infected, or reddened skin
on moles, birthmarks, warts with hair, genital warts, warts on the face, or on mucous membranes
if you have diabetes or poor blood circulation

DOSAGE AND ADMINISTRATION

adults and children 2 years and over:
wash affected area (optional: soak wart in warm water for 5 minutes).
dry area thoroughly.
apply one drop/small amount at a time with applicator/brush to sufficiently cover each wart
let dry
repeat once or twice daily as needed (until wart is removed) for up to 12 weeks
children under 2 years: ask a doctor

INACTIVE INGREDIENT

Glycerin, Polyethylene Glycol, Water, Borneol.